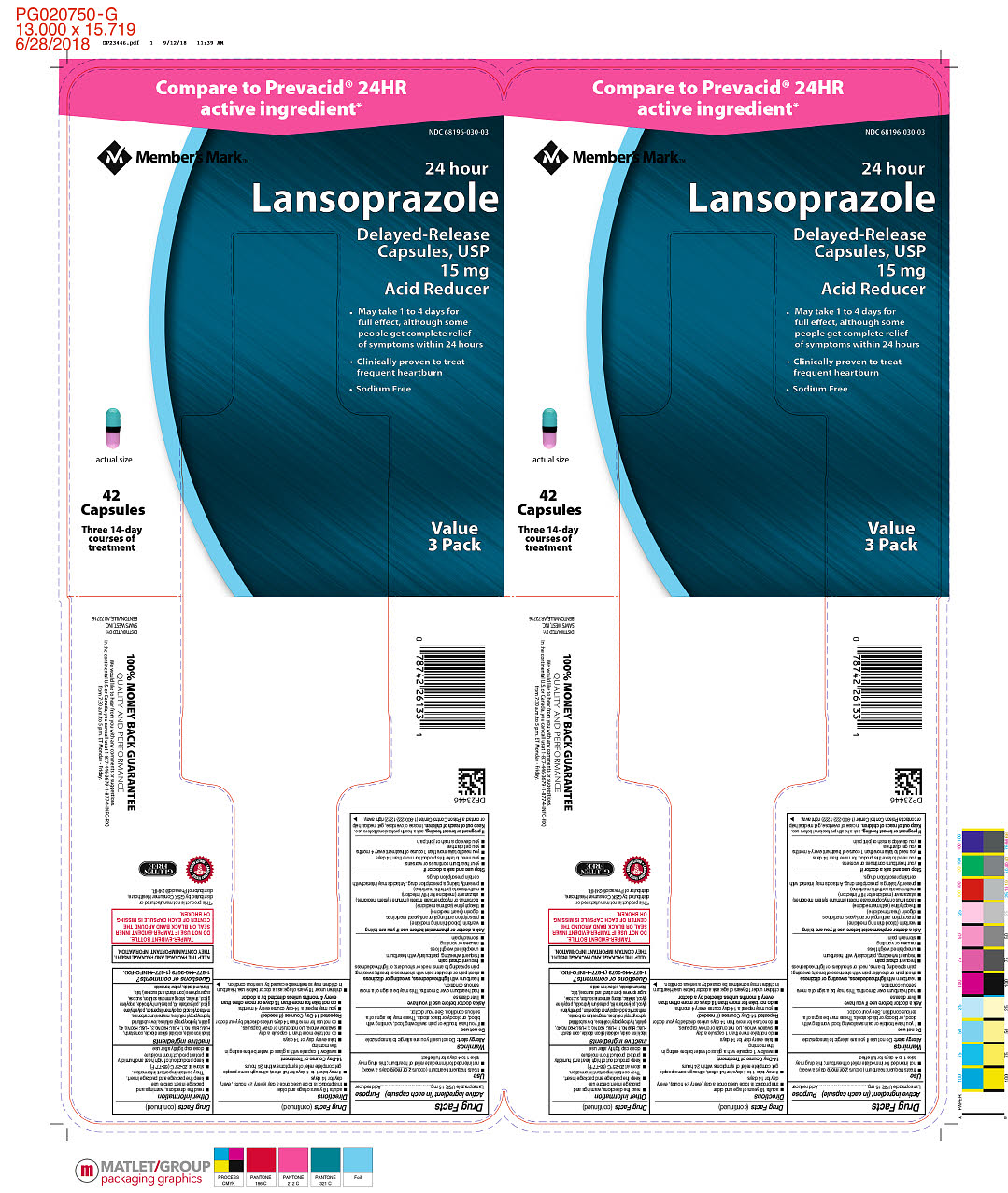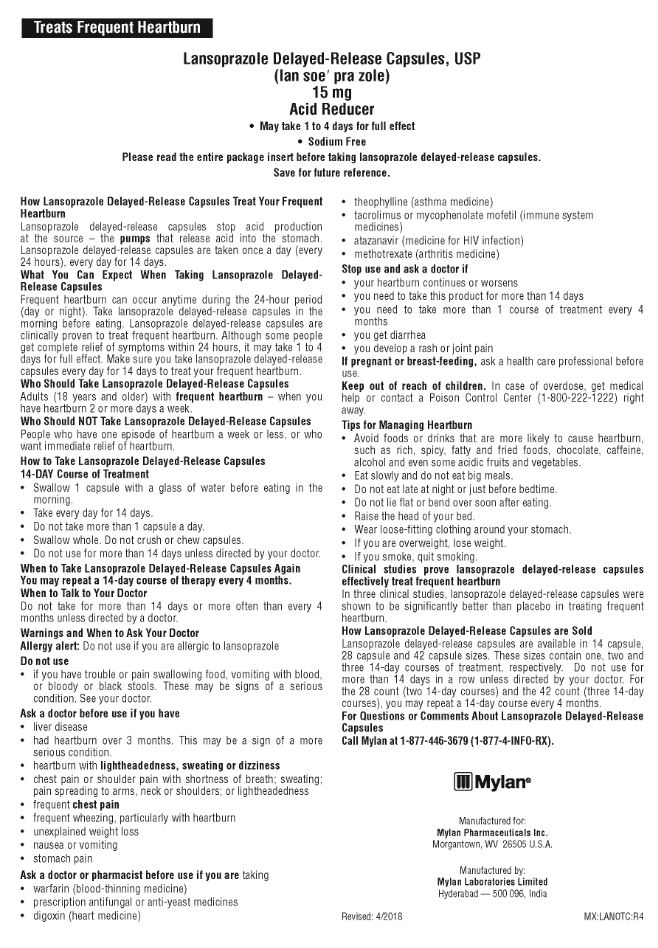 DRUG LABEL: Lansoprazole
NDC: 68196-030 | Form: CAPSULE, DELAYED RELEASE
Manufacturer: Sam's West, Inc.
Category: otc | Type: HUMAN OTC DRUG LABEL
Date: 20180924

ACTIVE INGREDIENTS: LANSOPRAZOLE 15 mg/1 1
INACTIVE INGREDIENTS: MAGNESIUM CARBONATE; STARCH, CORN; FERROSOFERRIC OXIDE; SILICON DIOXIDE; FD&C BLUE NO. 1; FD&C RED NO. 3; FD&C RED NO. 40; GELATIN; HYDROXYPROPYL CELLULOSE, LOW SUBSTITUTED; METHACRYLIC ACID - ETHYL ACRYLATE COPOLYMER (1:1) TYPE A; POLYETHYLENE GLYCOL, UNSPECIFIED; POLYSORBATE 80; POTASSIUM HYDROXIDE; PROPYLENE GLYCOL; SHELLAC; SUCROSE; TALC; TITANIUM DIOXIDE; FERRIC OXIDE YELLOW; HYDROXYPROPYL CELLULOSE (1600000 WAMW); AMMONIA

Lansoprazole DR Capsules USP 15 mg

Active ingredient (in each capsule)

Lansoprazole USP, 15 mg

Purpose

Acid reducer

Use

- treats frequent heartburn (occurs 2 or more days a week)
- not intended for immediate relief of heartburn; this drug may take 1 to 4 days for full effect

Warnings

Allergy alert:

Do not use if you are allergic to lansoprazole

Do not use

- if you have trouble or pain swallowing food, vomiting with blood, or bloody or black stools. These may be signs of a serious condition. See your doctor.

Ask a doctor before use if you have

- liver disease
- had heartburn over 3 months. This may be a sign of a more serious condition
- heartburn with lightheadedness, sweating or dizziness
- chest pain or shoulder pain with shortness of breath; sweating; pain spreading to arms, neck or shoulders; or lightheadedness
- frequent chest pain
- frequent wheezing, particularly with heartburn
- unexplained weight loss
- nausea or vomiting
- stomach pain

Ask a doctor or pharmacist before use if you are taking

- warfarin (blood-thinning medicine)
- prescription antifungal or anti-yeast medicines
- digoxin (heart medicine)
- theophylline (asthma medicine)
- tacrolimus or mycophenolate mofetil (immune system medicines)
- atazanavir (medicine for HIV infection)
- methotrexate (arthritis medicine)
- presently taking a prescription drug. Antacids may interact with certain prescription drugs.

Stop use and ask a doctor if

- your heartburn continues or worsens
- you need to take this product for more than 14 days
- you need to take more than 1 course of treatment every 4 months
- you get diarrhea
- you develop a rash or joint pain

If pregnant or breast-feeding,

ask a health professional before use.

Keep out of reach of children.

In case of overdose, get medical help or contact a Poison Control Center (1-800-222-1222) right away.

Directions

- adults 18 years of age and older
- this product is to be used once a day (every 24 hours), every day for 14 days
- it may take 1 to 4 days for full effect, although some people get complete relief of symptoms within 24 hours

14-Day Course of Treatment

- swallow 1 capsule with a glass of water before eating in the morning
- take every day for 14 days
- do not take more than 1 capsule a day
- swallow whole. Do not crush or chew capsules.
- do not use for more than 14 days unless directed by your doctor

Repeated 14-Day Courses (if needed)

- you may repeat a 14-day course every 4 months

- do not take for more than 14 days or more often than every 4 months unless directed by a doctor

- children under 18 years of age: ask a doctor before use. Heartburn in children may sometimes be caused by a serious condition.

Other information

- read the directions, warnings and package insert before use
- keep the package and package insert. They contain important information.
- store at 20-25ºC (68-77ºF).
- keep product out of high heat and humidity
- protect product from moisture
- close cap tightly after use

Inactive ingredients

black iron oxide, colloidal silicon dioxide, corn starch, FD&C Blue No. 1, FD&C Red No. 3, FD&C Red No. 40, gelatin, hydroxypropyl cellulose, low substituted hydroxypropyl cellulose, magnesium carbonate, methacrylic acid copolymer dispersion, polyethylene glycol, polysorbate 80, potassium hydroxide, propylene glycol, shellac, strong ammonia solution, sucrose, sugar spheres (corn starch and sucrose), talc, titanium dioxide, yellow iron oxide

Questions or comments?

1-877-446-3679 (1-877-4-INFO-RX).

Consumer Information

Treats Frequent Heartburn

LANSOPRAZOLE DELAYED-RELEASE CAPSULES, USP

(lan soe′ pra zole)

15 mg

Acid Reducer

• May take 1 to 4 days for full effect

• Sodium Free

Please read the entire package insert before taking lansoprazole delayed-release capsules.

Save for future reference.

How Lansoprazole Delayed-Release Capsules Treat Your Frequent Heartburn

Lansoprazole delayed-release capsules stop acid production at the source – the pumps that release acid into the stomach. Lansoprazole delayed-release capsules are taken once a day (every 24 hours), every day for 14 days.

What You Can Expect When Taking Lansoprazole Delayed-Release Capsules

Frequent heartburn can occur anytime during the 24-hour period (day or night). Take lansoprazole delayed-release capsules in the morning before eating. Lansoprazole delayed-release capsules are clinically proven to treat frequent heartburn. Although some people get complete relief of symptoms within 24 hours, it may take 1 to 4 days for full effect. Make sure you take lansoprazole delayed-release capsules every day for 14 days to treat your frequent heartburn.

Who Should Take Lansoprazole Delayed-Release Capsules

Adults (18 years and older) with frequent heartburn – when you have heartburn 2 or more days a week.

Who Should NOT Take Lansoprazole Delayed-Release Capsules

People who have one episode of heartburn a week or less, or who want immediate relief of heartburn.

How to Take Lansoprazole Delayed-Release Capsules 14-Day Course of Treatment

• Swallow 1 capsule with a glass of water before eating in the morning.

• Take every day for 14 days.

• Do not take more than 1 capsule a day.

• Swallow whole. Do not crush or chew capsules.

• Do not use for more than 14 days unless directed by your doctor.

When to Take Lansoprazole Delayed-Release Capsules Again

You may repeat a 14-day course of therapy every 4 months.

When to Talk to Your Doctor

Do not take for more than 14 days or more often than every 4 months unless directed by a doctor.

Warnings and When to Ask Your Doctor

Allergy alert: Do not use if you are allergic to lansoprazole.

Do not use

• if you have trouble or pain swallowing food, vomiting with blood, or bloody or black stools. These may be signs of a serious condition. See your doctor.

Ask your doctor before use if you have

• liver disease

• had heartburn over 3 months. This may be a sign of a more serious condition.

• heartburn with lightheadedness, sweating or dizziness

• chest pain or shoulder pain with shortness of breath; sweating; pain spreading to arms, neck or shoulders; or lightheadedness

• frequent chest pain

• frequent wheezing, particularly with heartburn

• unexplained weight loss

• nausea or vomiting

• stomach pain

Ask a doctor or pharmacist before use if you are taking

• warfarin (blood-thinning medicine)

• prescription antifungal or anti-yeast medicines

• digoxin (heart medicine)

• theophylline (asthma medicine)

• tacrolimus or mycophenolate mofetil (immune system medicines)

• atazanavir (medicine for HIV infection)

• methotrexate (arthritis medicine)

Stop use and ask a doctor if

• your heartburn continues or worsens

• you need to take this product for more than 14 days

• you need to take more than 1 course of treatment every 4 months

• you get diarrhea

• you develop a rash or joint pain

If pregnant or breast-feeding, ask a health professional before use.

Keep out of reach of children. In case of overdose, get medical help or contact a Poison Control Center (1-800-222-1222) right away.

Tips for Managing Heartburn

• Avoid foods or drinks that are more likely to cause heartburn, such as rich, spicy, fatty and fried foods, chocolate, caffeine, alcohol and even some acidic fruits and vegetables.

• Eat slowly and do not eat big meals.

• Do not eat late at night or just before bedtime.

• Do not lie flat or bend over soon after eating.

• Raise the head of your bed.

• Wear loose-fitting clothing around your stomach.

• If you are overweight, lose weight.

• If you smoke, quit smoking.

Clinical studies prove lansoprazole delayed-release capsules effectively treat frequent heartburn

In three clinical studies, lansoprazole delayed-release capsules were shown to be significantly better than placebo in treating frequent heartburn.

How Lansoprazole Delayed-Release Capsules are Sold

Lansoprazole delayed-release capsules are available in 14 capsule, 28 capsule and 42 capsule sizes. These sizes contain one, two and three 14-day courses of treatment, respectively. Do not use for more than 14 days in a row unless directed by your doctor. For the 28 count (two 14-day courses) and the 42 count (three 14-day courses), you may repeat a 14-day course every 4 months.

For Questions or Comments About Lansoprazole Delayed-Release Capsules

Call Mylan at 1-877-446-3679 (1-877-4-INFO-RX).

Revised: 4/2018

PRINCIPAL DISPLAY PANEL

Compare to Prevacid® 24HR active ingredient*

NDC 68196-030-03

Member's MarkTM

24 hour

Lansoprazole Delayed-Release Capsules, USP 15 mg

Acid Reducer

- May take 1 to 4 days for full effect, although some people get complete relief of symptoms within 24 hours
- Clinically proven to treat frequent heartburn
- Sodium Free

Value 3 Pack

actual size

42 Capsules

Three 14-day courses of treatment

KEEP THE PACKAGE AND PACKAGE INSERT. THEY CONTAIN IMPORTANT INFORMATION.

TAMPER-EVIDENT BOTTLE. DO NOT USE IF TAMPER-EVIDENT INNER OR BLACK BAND AROUND THE CENTER OF EACH CAPSULE IS MISSING OR BROKEN.

*This product is not manufactured or distributed by GSK Consumer Healthcare, distributor of Prevacid® 24HR.

LABORATORY TESTED - QUALITY ASSURED

GLUTEN FREE

100% MONEY BACK GUARANTEE

QUALITY AND PERFORMANCE

We would like to hear from you with any comments or suggestions.

In the continental U.S. or Canada, you can call us at 1-877-446-3679 (1-877-4-INFO-RX)

from 7:30 a.m. to 5 p.m. ET Monday - Friday.

DISTRIBUTED BY:

SAM'S WEST, INC.

BENTONVILLE, AR 72716

DP23446 Lansoprazole DR Capsules USP 15 mg

PRINCIPAL DISPLAY PANEL

Lansoprazole Insert DP23064